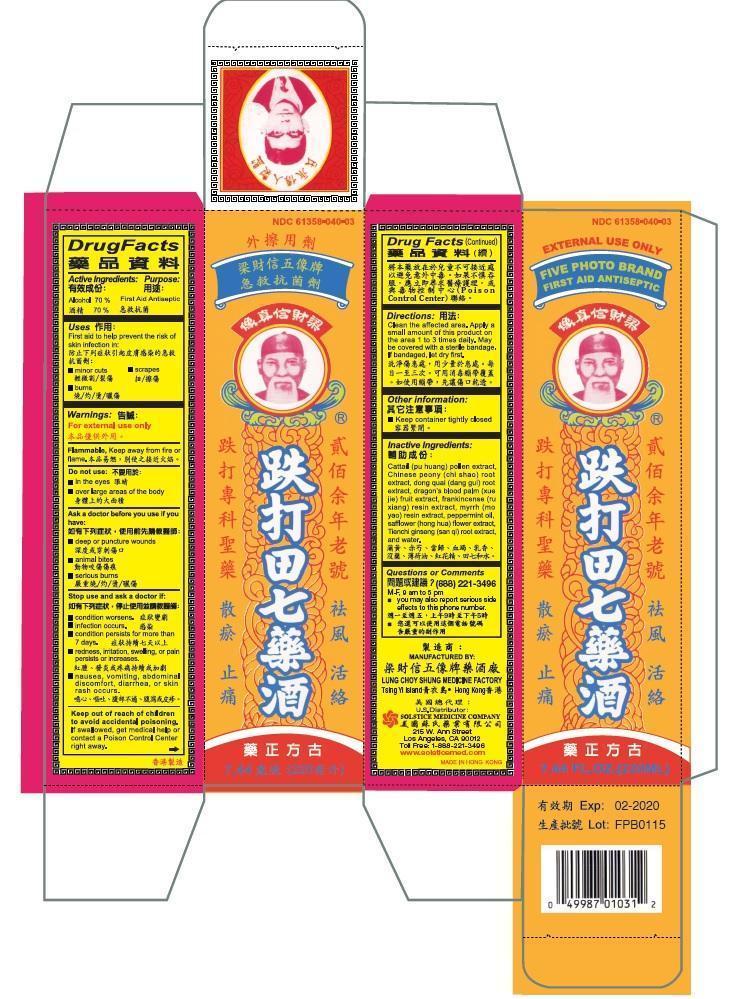 DRUG LABEL: FIVE PHOTO BRAND FIRST AID ANTISEPTIC
NDC: 61358-040 | Form: LIQUID
Manufacturer: LUNG CHOY SHUNG FIVE PHOTOS BRAND MEDICINE FTY
Category: otc | Type: HUMAN OTC DRUG LABEL
Date: 20191113

ACTIVE INGREDIENTS: ALCOHOL 70 g/100 mL
INACTIVE INGREDIENTS: TYPHA LATIFOLIA POLLEN; PAEONIA LACTIFLORA ROOT; ANGELICA SINENSIS ROOT; DAEMONOROPS DRACO RESIN; FRANKINCENSE; MYRRH; PEPPERMINT OIL; SAFFLOWER; PANAX NOTOGINSENG ROOT; WATER

DRUG FACTS

Active Ingredients
Alcohol 70%

Purpose
First Aid Antiseptic

Uses
First aid to help prevent the risk of skin infection in:
minor cuts
scrapes
burns

Warning
For external use only
Flammable, keep away from fire or flame.

Do not use
in the eyes
over large areas of the body

Ask doctor before you use if you have
deep or punter wounds
animal bites
serious burns

Stop use and ask doctor if
condition worsens
condition persists for more than 7 days
redness, irritation, swelling, or pain persists or increases
nausea, vomiting, abdominal discomfort, diarrhea, or skin rash occurs
infection occurs

Keep out of reach of children. If swallowed, get medical help or contact a Poison Control Center right away.

Directions
Clean the affected area. Apply a small amount of this product on the area 1 to 3 times daily. May be covered with a sterile bandage. If bandaged, let dry first.

Other Information
keep container tightly closed

Inactive Ingredients
Cattail (pu huang) pollen extract, Chinese peony (chi shao) root extract, costus (mu xiang) root extract, dong quai (dang gui) root extract, dragon’s blood palm (xue jie) fruit extract, frankincense (ru xiang) resin extract, myrrh (mo yao) resin extract, peppermint oil, saffflower (hong hua) flower extract, Tienchi ginseng (san qi) root extract, and water.

Questions or comments? (888) 221-3496 M-F 9am to 5pm

you may also report serious side effects to this phone number

PACKAGE LABEL

FIVE PHOTO BRAND FIRST AID ANTISEPTIC
NDC 61358-040-04
7.44 FL OZ (220 ML)